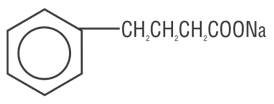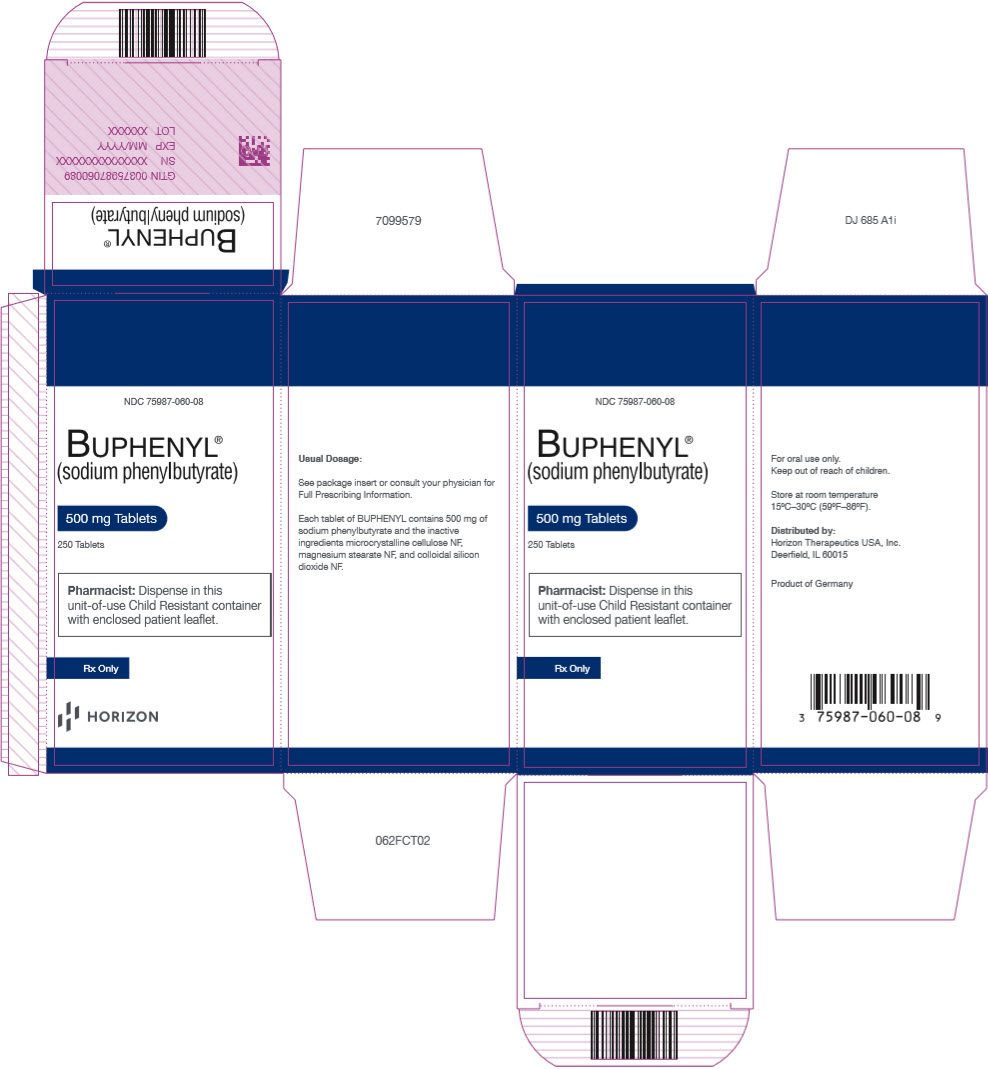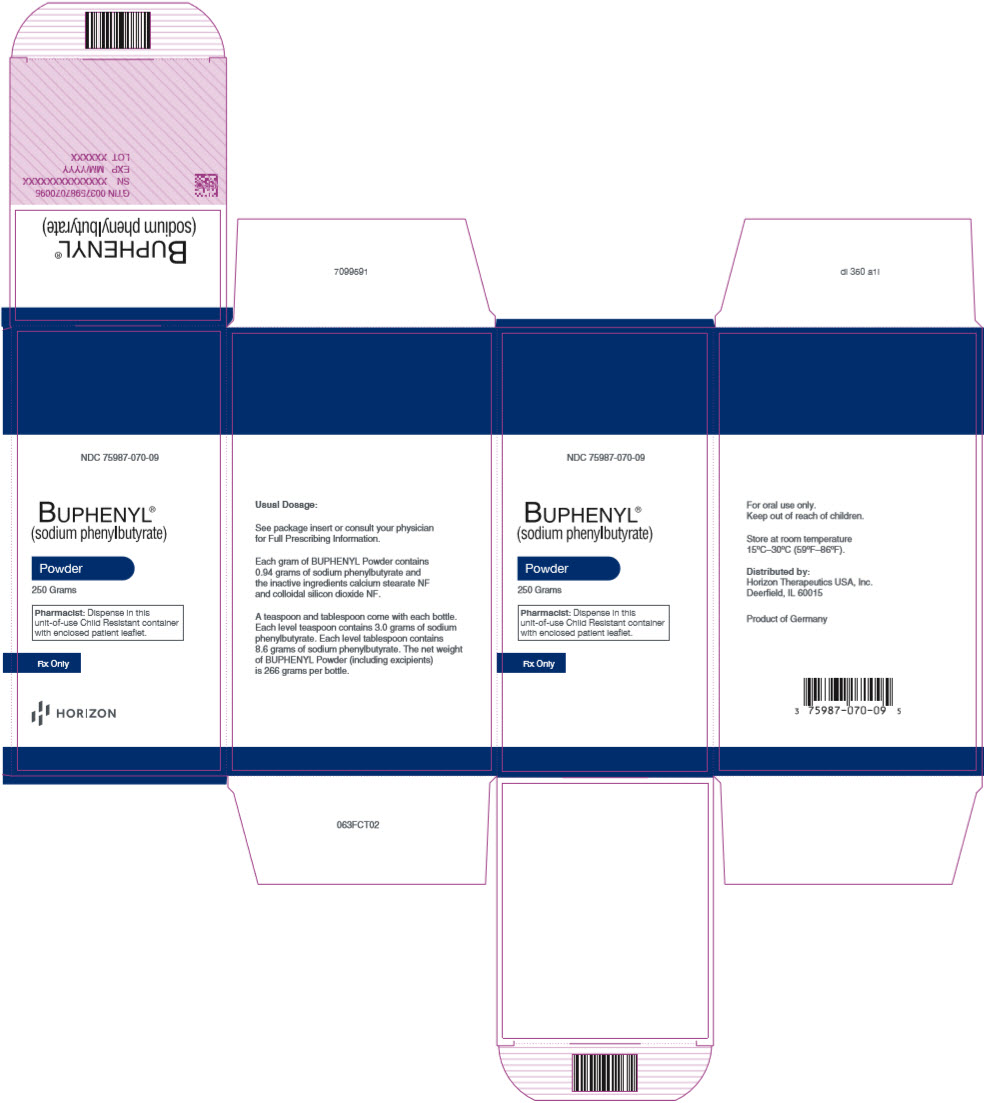 DRUG LABEL: BUPHENYL
NDC: 75987-060 | Form: TABLET
Manufacturer: Horizon Therapeutics USA, Inc.
Category: prescription | Type: HUMAN PRESCRIPTION DRUG LABEL
Date: 20241030

ACTIVE INGREDIENTS: SODIUM PHENYLBUTYRATE 500 mg/1 1
INACTIVE INGREDIENTS: MICROCRYSTALLINE CELLULOSE; SILICON DIOXIDE; MAGNESIUM STEARATE

BUPHENYL® (sodium phenylbutyrate) Tablets
BUPHENYL® (sodium phenylbutyrate) Powder

[bu'fen-əl]
(sodium phenylbutyrate)

Rx Only

DESCRIPTION

BUPHENYL (sodium phenylbutyrate) Tablets for oral administration and BUPHENYL (sodium phenylbutyrate) Powder for oral, nasogastric, or gastrostomy tube administration contain sodium phenylbutyrate. Sodium phenylbutyrate is an off-white crystalline substance which is soluble in water and has a strong salty taste. Sodium phenylbutyrate also is freely soluble in methanol and practically insoluble in acetone and diethyl ether. It is known chemically as 4-phenylbutyric acid, sodium salt with a molecular weight of 186 and the molecular formula C10H11O2Na.

Chemical Structure:

Each tablet of BUPHENYL contains 500 mg of sodium phenylbutyrate and the inactive ingredients microcrystalline cellulose NF, magnesium stearate NF, and colloidal silicon dioxide NF.

Each gram of BUPHENYL Powder contains 0.94 grams of sodium phenylbutyrate and the inactive ingredients calcium stearate NF, and colloidal silicon dioxide NF.

CLINICAL PHARMACOLOGY

Sodium phenylbutyrate is a pro-drug and is rapidly metabolized to phenylacetate. Phenylacetate is a metabolically active compound that conjugates with glutamine via acetylation to form phenylacetylglutamine. Phenylacetylglutamine then is excreted by the kidneys. On a molar basis, it is comparable to urea (each containing two moles of nitrogen). Therefore, phenylacetylglutamine provides an alternate vehicle for waste nitrogen excretion.

PHARMACOKINETICS

General

Pharmacokinetic studies have not been conducted in the primary patient population (neonates, infants, and children), but pharmacokinetic data were obtained from normal adult subjects.

Absorption

Peak plasma levels of phenylbutyrate occur within 1 hour after a single dose of 5 grams of sodium phenylbutyrate tablet with a Cmax of 218 µg/mL under fasting conditions; peak plasma levels of phenylbutyrate occur within 1 hour after a single dose of 5 grams of sodium phenylbutyrate powder with a Cmax of 195 µg/mL under fasting conditions. The effect of food on phenylbutyrate's absorption is unknown.

Disposition

The overall disposition of sodium phenylbutyrate and its metabolites has not been characterized fully. However, the drug is known to be metabolized to phenylacetate and subsequently to phenylacetylglutamine. Following oral administration of 5 grams (tablets), measurable plasma levels of phenylbutyrate and phenylacetate were detected 15 and 30 minutes after dosing, respectively, and phenylacetylglutamine was detected shortly thereafter. The pharmacokinetic parameters for phenylbutyrate for Cmax (µg/mL), Tmax (hours), and elimination half-life (hours) were 218, 1.35, and 0.77, respectively, and for phenylacetate were 48.5, 3.74, and 1.15, respectively.

Following oral administration of 5 grams of the powder, measurable plasma levels of phenylbutyrate and phenylacetate were detected 15 and 30 minutes after dosing, respectively, and phenylacetylglutamine was detected shortly thereafter. The pharmacokinetic parameters for phenylbutyrate for Cmax (µg/mL), Tmax (hours), and elimination half-life (hours) were 195, 1.00, and 0.76, respectively, and for phenylacetate were 45.3, 3.55, and 1.29, respectively.

The major sites for metabolism of sodium phenylbutyrate are the liver and kidney.

Excretion

A majority of the administered compound (approximately 80–100%) was excreted by the kidneys within 24 hours as the conjugation product, phenylacetylglutamine. For each gram of sodium phenylbutyrate administered, it is estimated that between 0.12–0.15 grams of phenylacetylglutamine nitrogen are produced.

Pharmacodynamics

In patients with urea cycle disorders, BUPHENYL decreased elevated plasma ammonia glutamine levels. It increases waste nitrogen excretion in the form of phenylacetylglutamine.

Special Populations

Gender

Significant gender differences were found in the pharmacokinetics of phenylbutyrate and phenylacetate, but not for phenylacetylglutamine. The pharmacokinetic parameters (AUC and Cmax), for both plasma phenylbutyrate and phenylacetate were about 30 to 50 percent greater in females than in males.

Hepatic insufficiency

In patients who did not have urea cycle disorders but had impaired hepatic function, the metabolism and excretion of sodium phenylbutyrate were not affected. However, this information was obtained from unvalidated, uncontrolled case studies.

INDICATIONS AND USAGE

BUPHENYL is indicated as adjunctive therapy in the chronic management of patients with urea cycle disorders involving deficiencies of carbamoyl phosphate synthetase (CPS), ornithine transcarbamylase (OTC), or argininosuccinic acid synthetase (AS). It is indicated in all patients with neonatal-onset deficiency (complete enzymatic deficiency, presenting within the first 28 days of life). It is also indicated in patients with late-onset disease (partial enzymatic deficiency, presenting after the first month of life) who have a history of hyperammonemic encephalopathy. It is important that the diagnosis be made early and treatment initiated immediately to improve survival. Any episode of acute hyperammonemia should be treated as a life-threatening emergency.

BUPHENYL must be combined with dietary protein restriction and, in some cases, essential amino acid supplementation. (See Nutritional Supplementation subsection of the DOSAGE AND ADMINISTRATION section.)

Previously, neonatal-onset disease was almost universally fatal within the first year of life, even when treated with peritoneal dialysis and essential amino acids or their nitrogen-free analogs. However, with hemodialysis, use of alternative waste nitrogen excretion pathways (sodium phenylbutyrate, sodium benzoate, and sodium phenylacetate), dietary protein restriction, and, in some cases, essential amino acid supplementation, the survival rate in newborns diagnosed after birth but within the first month of life is almost 80%. Most deaths have occurred during an episode of acute hyperammonemic encephalopathy. Patients with neonatal-onset disease have a high incidence of mental retardation. Those who had IQ tests administered had an incidence of mental retardation as follows: ornithine transcarbamylase deficiency, 100% (14/14 patients tested); argininosuccinic acid synthetase deficiency, 88% (15/17 patients tested); and carbamoyl phosphate synthetase deficiency, 57% (4/7 patients tested). Retardation was severe in the majority of the retarded patients.

In patients diagnosed during gestation and treated prior to any episode of hyperammonemic encephalopathy, survival is 100%, but even in these patients, most subsequently demonstrate cognitive impairment or other neurologic deficits.

In late-onset deficiency patients, including females heterozygous for ornithine transcarbamylase deficiency, who recover from hyperammonemic encephalopathy and are then treated chronically with sodium phenylbutyrate and dietary protein restriction, the survival rate is 98%. The two deaths in this group of patients occurred during episodes of hyperammonemic encephalopathy. However, compliance with the therapeutic regimen has not been adequately documented to allow evaluation of the potential for BUPHENYL and dietary protein restriction to prevent mental deterioration and recurrence of hyperammonemic encephalopathy if carefully adhered to. The majority of these patients tested (30/46 or 65%) have IQ's in the average to low average/borderline mentally retarded range. Reversal of preexisting neurologic impairment is not likely to occur with treatment and neurologic deterioration may continue in some patients.

Even on therapy, acute hyperammonemic encephalopathy recurred in the majority of patients for whom the drug is indicated.

BUPHENYL may be required lifelong unless orthotopic liver transplantation is elected.

(See CLINICAL PHARMACOLOGY, Pharmacodynamics subsection for the biochemical effects of BUPHENYL).

CONTRAINDICATIONS

BUPHENYL should not be used to manage acute hyperammonemia, which is a medical emergency.

WARNINGS

Each BUPHENYL Tablet contains 62 mg of sodium (9.2% w/w) (corresponding to 124 mg of sodium per gram of sodium phenylbutyrate [12.4% w/w]) and BUPHENYL Powder contains 11.7 grams of sodium per 100 grams of powder, corresponding to 125 mg of sodium per gram of sodium phenylbutyrate (12.4% w/w). BUPHENYL should be used with great care, if at all, in patients with congestive heart failure or severe renal insufficiency, and in clinical states in which there is sodium retention with edema.

Because BUPHENYL is metabolized in the liver and kidney, and phenylacetylglutamine is primarily excreted by the kidney, use caution when administering the drug to patients with hepatic or renal insufficiency or inborn errors of beta oxidation. Probenecid is known to inhibit the renal transport of many organic compounds, including hippuric acid, and may affect renal excretion of the conjugated product of BUPHENYL as well as its metabolite.

Use of corticosteroids may cause the breakdown of body protein and increase plasma ammonia levels.

PRECAUTIONS

General

BUPHENYL should not be administered to patients with known hypersensitivity to sodium phenylbutyrate or any component of this preparation.

There have been published reports of hyperammonemia being induced by haloperidol and by valproic acid.

Neurotoxicity of phenylacetate in animals

When given subcutaneously to rat pups, 190–474 mg/kg phenylacetate caused decreased proliferation and increased loss of neurons, and it reduced CNS myelin. Cerebral synapse maturation was retarded, and the number of functioning nerve terminals in the cerebrum was reduced, which resulted in impaired brain growth. Prenatal exposure of rat pups to phenylacetate produced lesions in layer 5 of the cortical pyramidal cells; dendritic spines were longer and thinner than normal and reduced in number.

Information for Patients

The full text of the separate insert of information for patients is reprinted at the end of the labeling.

Laboratory Tests

Plasma levels of ammonia, arginine, branched-chain amino acids, and serum proteins should be maintained within normal limits, and plasma glutamine should be maintained at levels less than 1,000 µmol/L. Serum drug levels of phenylbutyrate and its metabolites, phenylacetate and phenylacetylglutamine, should be monitored periodically.

Carcinogenesis, Mutagenesis, Impairment of Fertility

Carcinogenicity, mutagenicity, and fertility studies of sodium phenylbutyrate have not been conducted.

Pregnancy

Animal reproduction studies have not been conducted with BUPHENYL. It is also not known whether BUPHENYL can cause fetal harm when administered to a pregnant woman or can affect reproduction capacity.

BUPHENYL should be given to a pregnant woman only if clearly needed.

Nursing Mothers

It is not known whether this drug is excreted in human milk. Because many drugs are excreted in human milk, caution should be exercised when BUPHENYL is administered to a nursing woman.

Pediatric Use

The use of tablets for neonates, infants and children to the weight of 20 kg is not recommended. (See Dosage and Administration.)

ADVERSE REACTIONS

The assessment of clinical adverse events came from 206 patients treated with sodium phenylbutyrate. Adverse events (both clinical and laboratory) were not collected systematically in these patients, but were obtained from patient visit reports by the 65 co-investigators. Causality of adverse effects is sometimes difficult to determine in this patient population because they may result from either the underlying disease, the patient's restricted diet, intercurrent illness, or BUPHENYL. Furthermore, the rates may be underestimated because they were reported primarily by parent or guardian and not the patient.

Clinical Adverse Events

In female patients, the most common clinical adverse event reported was amenorrhea/menstrual dysfunction (irregular menstrual cycles), which occurred in 23% of the menstruating patients.

Decreased appetite occurred in 4% of all patients. Body odor (probably caused by the metabolite, phenylacetate) and bad taste or taste aversion were each reported in 3% of patients.

Other adverse events reported in 2% or fewer patients were:

Gastrointestinal: abdominal pain, gastritis, nausea and vomiting; constipation, rectal bleeding, peptic ulcer disease, and pancreatitis each occurred in one patient.

Hematologic: aplastic anemia and ecchymoses each occurred in one patient.

Cardiovascular: arrhythmia and edema each occurred in one patient.

Renal: renal tubular acidosis

Psychiatric: depression

Skin: rash

Miscellaneous: headache, syncope, and weight gain

Neurotoxicity was reported in cancer patients receiving intravenous phenylacetate, 250–300 mg/kg/day for 14 days, repeated at 4-week intervals. Manifestations were predominately somnolence, fatigue, and lightheadedness; with less frequent headache, dysgeusia, hypoacusis, disorientation, impaired memory, and exacerbation of a pre-existing neuropathy. These adverse events were mainly mild in severity. The acute onset and reversibility when the phenylacetate infusion was discontinued suggest a drug effect.

Laboratory Adverse Events

In patients with urea cycle disorders, the frequency of laboratory adverse events by body system were:

Metabolic: acidosis (14%), alkalosis and hyperchloremia (each 7%), hypophosphatemia (6%), hyperuricemia and hyperphosphatemia (each 2%), and hypernatremia and hypokalemia (each 1%).

Nutritional: hypoalbuminemia (11%) and decreased total protein (3%).

Hepatic: increased alkaline phosphatase (6%), increased liver transaminases (4%), and hyperbilirubinemia (1%).

Hematologic: anemia (9%), leukopenia and leukocytosis (each 4%), thrombocytopenia (3%), and thrombocytosis (1%).

The clinician is advised to routinely perform urinalysis, blood chemistry profiles, and hematologic tests.

OVERDOSAGE

Overdoses of BUPHENYL exceeding ten-fold the maximum recommended dosage may produce emesis, CNS depression, metabolic acidosis with or without respiratory alkalosis, hypernatremia, hypokalemia, and hypophosphatemia. Symptoms of overdose overlap with those of acute hyperammonemia. If overdose occurs, discontinue BUPHENYL, monitor plasma phenylacetate and ammonia levels closely, and institute appropriate emergency management, which may include hemodialysis, continuous veno-venous hemofiltration (CVVH), or extracorporeal membrane oxygenation (ECMO).

DOSAGE AND ADMINISTRATION

For oral use only.

The use of BUPHENYL Tablets is indicated for children weighing more than 20 kg and for adults.

The usual total daily dose of BUPHENYL Tablets and Powder for patients with urea cycle disorders is 450–600 mg/kg/day in patients weighing less than 20 kg, or 9.9–13.0 g/m2/day in larger patients. The tablets and powder are to be taken in equally divided amounts with each meal or feeding (i.e., three to six times per day).

BUPHENYL Powder is indicated for oral use (via mouth, gastrostomy, or nasogastric tube) only. The powder is to be mixed with food (solid or liquid) for immediate use; however, when dissolved in water, BUPHENYL Powder has been shown to be stable for up to one week at room temperature or refrigerated. Sodium phenylbutyrate is very soluble in water (5 grams per 10 mL). When BUPHENYL Powder is added to a liquid, only sodium phenylbutyrate will dissolve, the excipients will not. The effect of food on sodium phenylbutyrate has not been determined.

Each level teaspoon (enclosed) dispenses 3.2 grams of powder and 3.0 grams of sodium phenylbutyrate. Each level tablespoon (enclosed) dispenses 9.1 grams of powder and 8.6 grams of sodium phenylbutyrate.

Shake lightly before use.

The safety or efficacy of doses in excess of 20 grams (40 tablets) per day has not been established.

NUTRITIONAL MANAGEMENT

To promote growth and development, plasma levels of ammonia, arginine, branched-chain amino acids, and serum protein should be maintained within normal limits while plasma glutamine is maintained at levels less than 1,000 µmol/L. Minimum daily protein intake for a patient of a particular age should be taken from, for example, "Recommended Dietary Allowances", 10th ed., Food and Nutrition Board, National Academy of Sciences, 1989. The allocation of dietary nitrogen into natural protein and essential amino acids is a function of age, residual urea cycle enzyme activity, and the dose of sodium phenylbutyrate.

At the recommended dose of sodium phenylbutyrate, it is suggested that infants with neonatal-onset CPS and OTC deficiencies initially receive a daily dietary protein intake limited to approximately 1.6 g/kg/day for the first 4 months of life. If tolerated, the daily protein intake may be increased to 1.9 g/kg/day during this period. Protein tolerance will decrease as the growth rate decreases, requiring a reduction in dietary nitrogen intake. From 4 months to 1 year of age, it is recommended that the infant receive at least 1.4 g/kg/day, but 1.7 g/kg/day is advisable. From 1 to 3 years of age, the protein intake should not be less than 1.2 g/kg/day; 1.4 g/kg/day is advisable during this period. For neonatal-onset patients with carbamoyl phosphate synthetase deficiency or ornithine transcarbamylase deficiency who are at least 6 months of age, it is recommended that the daily protein intake be equally divided between natural protein and supplemental essential amino acids.

Patients with argininosuccinic acid synthetase deficiency and those with late-onset disease (partial deficiencies, including females heterozygous for ornithine transcarbamylase), initially may receive a diet containing the age-determined minimal daily natural protein allowance. The protein intake may be increased as tolerated and determined by plasma glutamine and other amino acid levels. However, many patients with partial deficiencies avoid dietary protein.

Citrulline supplementation is required and recommended for patients diagnosed with neonatal-onset deficiency of carbamoyl phosphate synthetase or ornithine transcarbamylase; citrulline daily intake is recommended at 0.17 g/kg/day or 3.8 g/m^2/day.

The free-base form of arginine may be used instead of citrulline in patients with milder forms of carbamoyl phosphate synthetase and ornithine transcarbamylase deficiency (daily intake is recommended at 0.17 g/kg/day or 3.8 g/m^2/day).

Arginine supplementation is needed for patients diagnosed with deficiency of argininosuccinic acid synthetase; arginine (free base) daily intake is recommended at 0.4–0.7 g/kg/day or 8.8–15.4 g/m^2/day.

If caloric supplementation is indicated, a protein-free product is recommended. Caloric intake should be based upon the "Recommended Dietary Allowances", 10th ed., Food and Nutrition Board, National Research Council, National Academy of Sciences, 1989.

HOW SUPPLIED

BUPHENYL Tablets are available in 250 cc bottles which contain 250 sodium phenylbutyrate tablets (NDC 75987-060-08). The bottles are equipped with child-resistant caps. Each tablet is off-white, oval, and embossed with "UCY 500". Each tablet contains 500 mg of sodium phenylbutyrate. STORE AT ROOM TEMPERATURE 15°C–30°C (59°F–86°F). AFTER OPENING, KEEP BOTTLE TIGHTLY CLOSED.

BUPHENYL Powder is available in 500 cc bottles, which hold 266 grams of powder, containing 250 grams of sodium phenylbutyrate (NDC 75987-070-09). The bottles are equipped with child-resistant caps. Measurers are provided. Each level teaspoon (enclosed) dispenses 3.2 grams of powder and 3.0 grams of sodium phenylbutyrate. Each level tablespoon (enclosed) dispenses 9.1 grams of powder and 8.6 grams of sodium phenylbutyrate. STORE AT ROOM TEMPERATURE 15ºC–30ºC (59ºF–86ºF). AFTER OPENING, KEEP BOTTLE TIGHTLY CLOSED.

Distributed by: Horizon Therapeutics USA, Inc. Deerfield, IL 60015.

Product of Germany

NDC 75987-060-08 bottle contains 250 tablets of 500 mg.
NDC 75987-070-09 bottle containing 250 g of sodium phenylbutyrate powder.

Prescribing Information as of March 2023.

BUP-US-PI-004

PATIENT PACKAGE INSERT

BUPHENYL® (sodium phenylbutyrate) Tablets

BUPHENYL® (sodium phenylbutyrate) Powder

What is the most important information I should know about BUPHENYL?

BUPHENYL is prescribed along with changes in diet for long-term treatment of urea cycle disorders. BUPHENYL can only be obtained with a prescription from your doctor.

BUPHENYL must be taken exactly as the doctor prescribes; do not increase or decrease the dose of this medication without the doctor's approval.

What are urea cycle disorders?

Urea cycle disorders include a group of diseases, each having a specific liver enzyme deficiency. Because they are inherited, other family members may be affected. These disorders vary in severity and may be first detected at various ages, from newborn infants to adults. They lead to increased amounts of ammonia in the blood, which may cause disturbed brain function and severe brain damage. Typical signs of the disease are decreased mental awareness, vomiting, combativeness, slurred speech, unstable gait, and unconsciousness. The diagnosis of urea cycle disorders requires special laboratory tests. These typical signs of the disease may recur after the diagnosis is made if the condition is not under control. If they do, the doctor should be notified immediately because this is a medical emergency. An infection can cause the condition to go out of control. Therefore, if a fever develops, the doctor should be seen immediately.

A patient or carrier of these disorders should wear a Medic Alert tag stating the diagnosis. In the event that the patient has a sudden, rapid accumulation of ammonia in the blood, and, therefore, in the brain, leading to unconsciousness, the doctor will be alerted to treat the disease properly.

Periodically, depending upon the severity of a particular patient's urea cycle disorder, it will be necessary to perform blood tests. These include plasma ammonia, plasma amino acid levels, and other more routine blood tests to evaluate nutritional status.

What is BUPHENYL?

BUPHENYL is a drug that helps to prevent ammonia from accumulating in the blood. BUPHENYL aids the body in eliminating substances that produce ammonia. However, despite drug treatment, blood ammonia levels may become elevated periodically and there may be episodes of altered brain function in association with these ammonia elevations. Patients who have disease onset as newborns have a high incidence of mental retardation. Medical attention should be obtained as soon as signs appear (see above under "What are urea cycle disorders?"). BUPHENYL may be used as lifelong therapy or as a temporary measure until liver transplantation is performed.

What diet should I or my child follow?

In addition to taking BUPHENYL, it is equally important that a prescribed diet be followed. Because there is great variability in the severity of urea cycle disorders, each patient's diet should be custom designed by a physician and a nutritionist. Because the diet is so important, it is recommended that the prescribed diet be discussed with a nutritionist who is familiar with urea cycle disorders.

Who should not take BUPHENYL?

BUPHENYL is prescribed only for patients with urea cycle disorders. It is not to be used for any other reason. Keep the medication in a safe place where children cannot reach it.

What other medical conditions may also be present that could increase the risk of taking BUPHENYL?

Heart failure or decreased kidney function may lead to retention of the sodium content of BUPHENYL with potentially serious consequences such as worsening heart failure, high blood pressure, and swelling. If these medical conditions are present, the doctor will determine if your child should take BUPHENYL.

How should I or my child take BUPHENYL?

The dose of BUPHENYL prescribed for adults and children is based upon the patient's weight or size. It is very important that the full amount prescribed for any 24-hour period be taken. If a dose is missed it should be administered as soon as possible that same day. The total daily dose should be administered in equally divided amounts with meals.

What medications should I or my child avoid or be cautious of taking while on BUPHENYL?

Patients with urea cycle disorders usually should not take Depakene® (valproic acid), a drug sometimes prescribed for seizure disorders, or Haldol® (haloperidol), a drug used to treat certain types of psychiatric or neurologic disorders. Both of these drugs have been reported to increase blood ammonia levels. Steroids may break down body protein, thereby increasing blood ammonia levels. The doctor should be consulted before administering medications containing steroids.

What medications may affect the way the body breaks down the drug?

Probenecid, a medication used to treat gout, may affect the way the kidneys excrete BUPHENYL (consult the doctor for details).

What are the most common side effects of BUPHENYL?

The most common side effect reported in premenopausal women taking BUPHENYL was absent or irregular menstrual periods. Decreased appetite was reported in 4% of all people treated. Body odor and bad taste were each reported in 3% of all patients treated.

A breakdown product of BUPHENYL has been associated mainly with sleepiness and light-headedness. Because these symptoms may also be due to the urea cycle going out of control, a doctor should see the patient immediately if these symptoms occur, so the cause can be determined. Blood tests should be performed periodically for adverse effects and for levels of medication and its breakdown products.

How should BUPHENYL be stored?

BUPHENYL should be stored in a tightly closed bottle at room temperature.

This leaflet provides a brief summary of the information available on BUPHENYL. The information here is incomplete and is not designed to take the place of your doctor's instructions. For more complete information, consult your physician, or contact Horizon at 1-866-479-6742.

BUP-US-PPI-004

PRINCIPAL DISPLAY PANEL - 500 mg Tablet Bottle Carton

NDC 75987-060-08

BUPHENYL®
(sodium phenylbutyrate)

500 mg Tablets

250 Tablets

Pharmacist: Dispense in this
unit-of-use Child Resistant container
with enclosed patient leaflet.

Rx Only

PRINCIPAL DISPLAY PANEL - 250 Gram Bottle Carton

NDC 75987-070-09

BUPHENYL®
(sodium phenylbutyrate)

Powder

250 Grams

Pharmacist: Dispense in this
unit-of-use Child Resistant container
with enclosed patient leaflet.

Rx Only